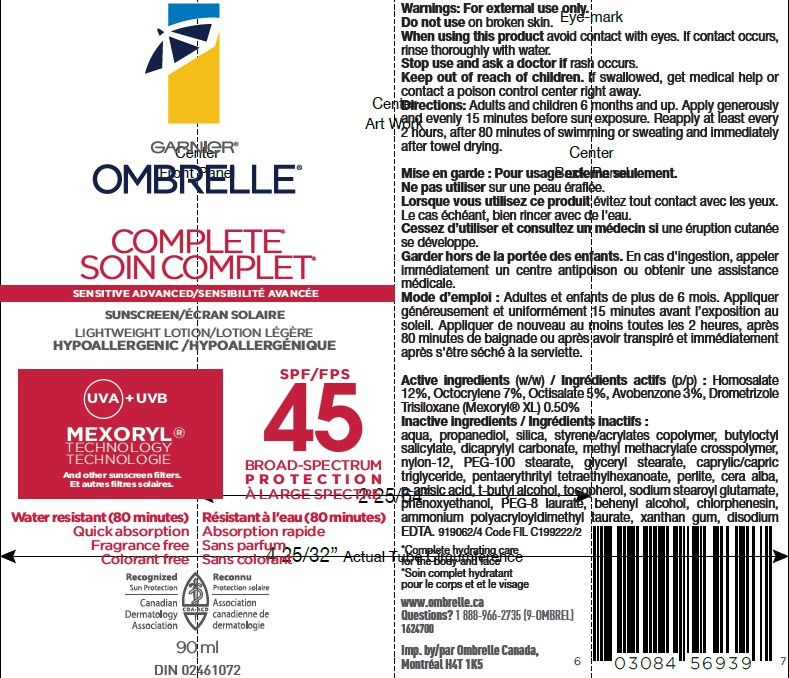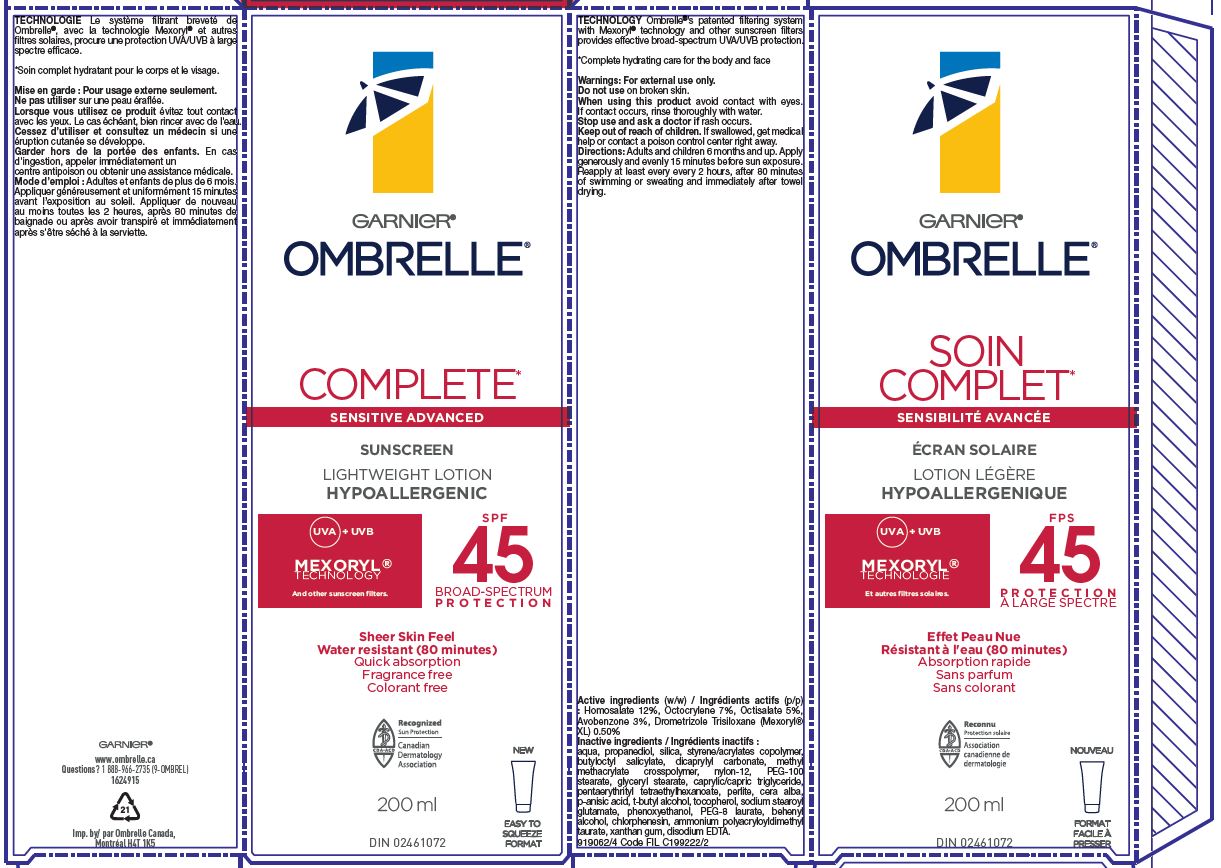 DRUG LABEL: Garnier Ombrelle Complete Sensitive Advanced Lightweight hypoallergenic SPF 45 Mexoryl Technology
NDC: 49967-397 | Form: LOTION
Manufacturer: L'Oreal USA Products Inc
Category: otc | Type: HUMAN OTC DRUG LABEL
Date: 20251209

ACTIVE INGREDIENTS: HOMOSALATE 120 mg/1 mL; OCTOCRYLENE 70 mg/1 mL; OCTISALATE 50 mg/1 mL; AVOBENZONE 30 mg/1 mL; DROMETRIZOLE TRISILOXANE 5 mg/1 mL
INACTIVE INGREDIENTS: WATER; PROPANEDIOL; SILICON DIOXIDE; BUTYLOCTYL SALICYLATE; DICAPRYLYL CARBONATE; METHYL METHACRYLATE/GLYCOL DIMETHACRYLATE CROSSPOLYMER; NYLON-12; PEG-100 STEARATE; GLYCERYL MONOSTEARATE; MEDIUM-CHAIN TRIGLYCERIDES; PENTAERYTHRITYL TETRAETHYLHEXANOATE; PERLITE; WHITE WAX; P-ANISIC ACID; TERT-BUTYL ALCOHOL; TOCOPHEROL; SODIUM STEAROYL GLUTAMATE; PHENOXYETHANOL; PEG-8 LAURATE; DOCOSANOL; CHLORPHENESIN; AMMONIUM POLYACRYLOYLDIMETHYL TAURATE (55000 MPA.S); XANTHAN GUM; EDETATE DISODIUM

Drug Facts

Active ingredients

Homosalate 12%

Octocrylene 7%

Octisalate 5%

Avobenzone 3%

Drometrizole Trisiloxane 0.5%

Inactive ingredients

aqua, propanediol, silica, styrene/acrylates copolymer, butyloctyl salicylate, dicaprylyl carbonate, methyl methacrylate copolymer, nylon-12, PEG-100 stearate, glyceryl stearate, caprylic/capric triglyceride, pentaerythrityl tetrathylhexanoate, perlite, cera alba, p-anisic acid, t-butyl alcohol, tocopherol, sodium stearoyl glutamate, phenoxyethanol, PEG-8 laurate, behenyl alcohol, chlorphenesin, ammonium polyacryloyldimethyl taurate, xanthan gum, disodium EDTA

Warnings

For external use only

Do not use

on damaged or broken skin

When using this product

avoid contact with eyes. If contact occurs, rinse thoroughly with water.

Stop use and ask a doctor if

rash occurs

Keep out of reach of children.

If swallowed, get medical help or contact a poison control center right away.

Directions

Adults and children 6 months and up. Apply generously and evenly 15 minutes before sun exposure. Reapply at least every 2 hours, after 80 minutes of swimming or sweating and immediately after towel drying.